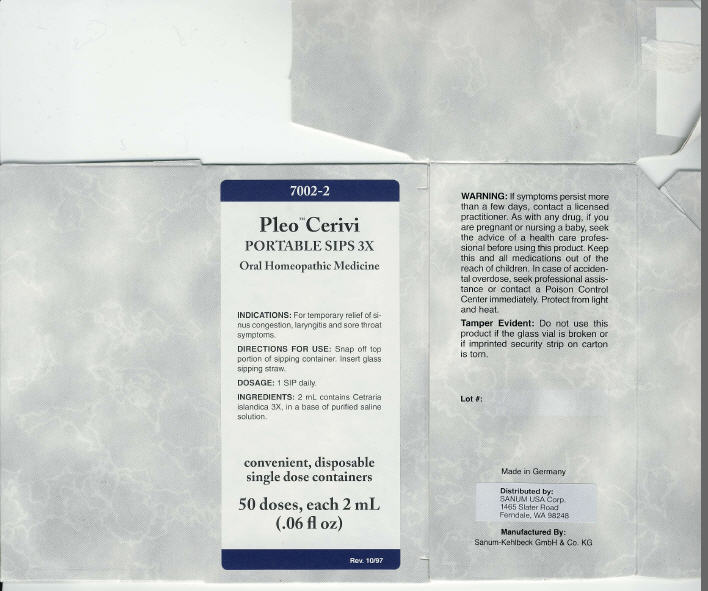 DRUG LABEL: Pleo Cerivi
NDC: 60681-7002 | Form: LIQUID
Manufacturer: Sanum Kehlbeck GmbH & Co. KG
Category: homeopathic | Type: HUMAN OTC DRUG LABEL
Date: 20091221

ACTIVE INGREDIENTS: Cetraria islandica subsp. islandica 3 [hp_X]/2 mL
INACTIVE INGREDIENTS: water; sodium chloride

Pleo™ Cerivi
PORTABLE SIPS 3X

Oral Homeopathic Medicine

50 doses, each 2 mL
(.06 fl oz)

INDICATIONS

For temporary relief of sinus congestion, laryngitis and sore throat symptoms.

DIRECTIONS FOR USE

Snap off top portion of sipping container. Insert glass sipping straw.

DOSAGE

1 SIP daily.

INGREDIENTS

2 mL contains Cetraria islandica 3X, in a base of purified saline solution.

WARNING

If symptoms persist more than a few days, contact a licensed practitioner. As with any drug, if you are pregnant or nursing a baby, seek the advice of a health care professional before using this product.

KEEP OUT OF REACH OF CHILDREN

Keep this and all medications out of the reach of children. In case of accidental overdose, seek professional assistance or contact a Poison Control Center immediately.

STORAGE AND HANDLING

Protect from light and heat.

Tamper Evident

Do not use this product if the glass vial is broken or if imprinted security strip on carton is torn.

Made in Germany

Distributed by:
SANUM USA Corp.
1465 Slater Road
Ferndale, WA 98248

Manufactured By:
Sanum-Kehlbeck GmbH & Co. KG

Rev. 10/97

PRINCIPAL DISPLAY PANEL - 2 mL Carton

7002-2

Pleo™ Cerivi
PORTABLE SIPS 3X

Oral Homeopathic Medicine

INDICATIONS: For temporary relief of si-
nus congestion, laryngitis and sore throat
symptoms.

DIRECTIONS FOR USE: Snap off top
portion of sipping container. Insert glass
sipping straw.

DOSAGE: 1 SIP daily

INGREDIENTS: 2 mL contains Cetraria
islandica 3X, in a base of purified saline
solution.

convenient, disposable
single dose containers

50 doses, each 2 mL
(.06 fl oz)

Rev. 10/97